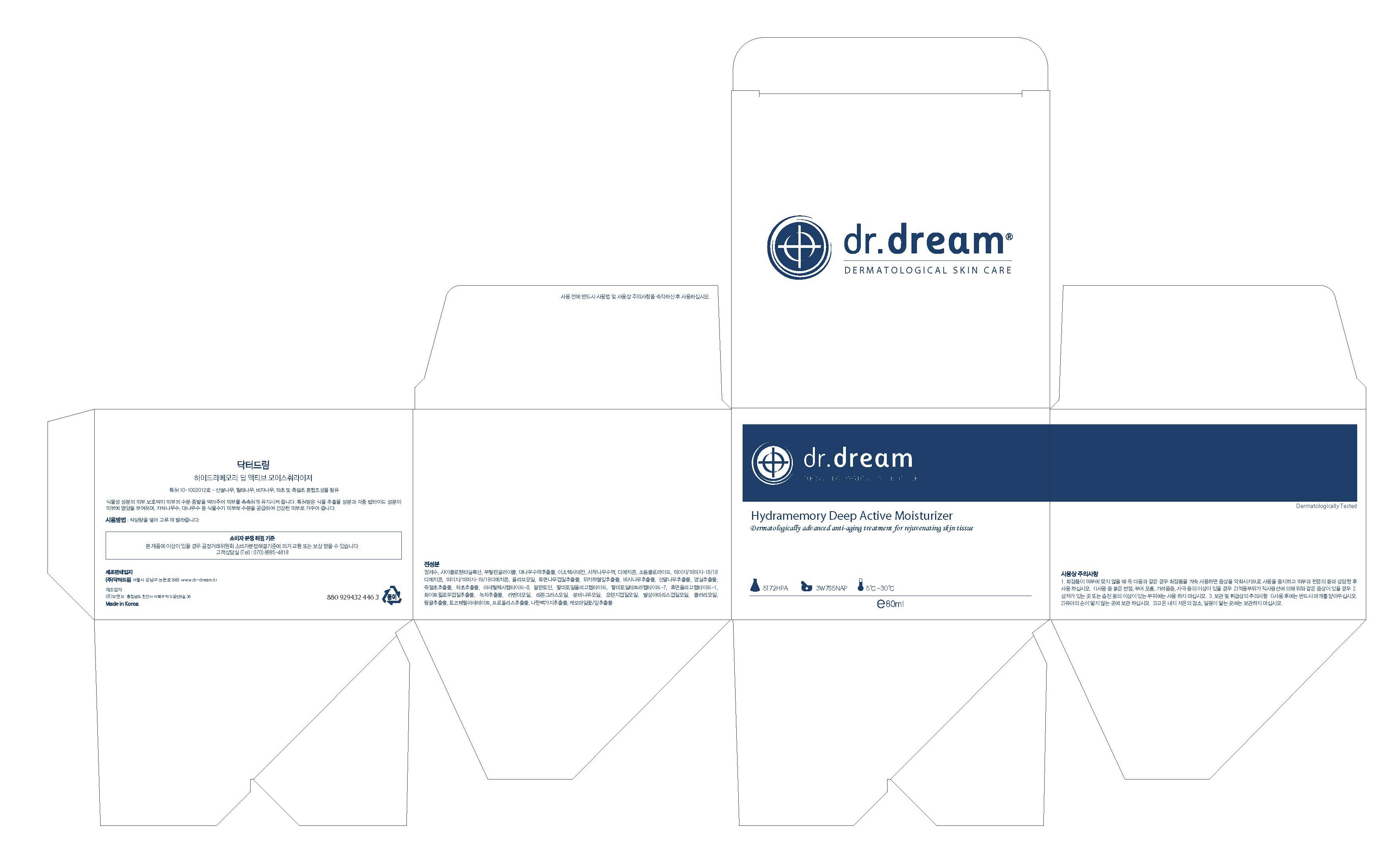 DRUG LABEL: Dr. Dream Hydramemory Deep active Moisturizer
NDC: 53077-6001 | Form: CREAM
Manufacturer: Dr. Dream Inc
Category: otc | Type: HUMAN OTC DRUG LABEL
Date: 20120925

ACTIVE INGREDIENTS: WITCH HAZEL 0.1 mg/100 mL
INACTIVE INGREDIENTS: PALMITOYL OLIGOPEPTIDE; PALMITOYL TETRAPEPTIDE-7; POLYSORBATE 60; GLYCERIN; CAPRYLHYDROXAMIC ACID; ADENOSINE; AMMONIUM ACRYLOYLDIMETHYLTAURATE/VP COPOLYMER; NEOPENTYL GLYCOL; BLACK OLIVE; SODIUM CHONDROITIN SULFATE (PORCINE; 5500 MW); LAVANDULA ANGUSTIFOLIA FLOWERING TOP; CYMBOPOGON SCHOENANTHUS OIL; ABIES SIBIRICA LEAF OIL; ORANGE; AMYRIS BALSAMIFERA OIL; CLARY SAGE OIL; LECITHIN, SOYBEAN; SODIUM PHOSPHATE; HYALURONATE SODIUM; THIOREDOXIN; PREZATIDE COPPER; PALMITOYL PENTAPEPTIDE-4; GLYCINE; GLUTAMINE; LYSINE; LEUCINE; METHIONINE; VALINE; SERINE; CYSTEINE; CYSTINE; ASPARAGINE; ALANINE; ARGININE; ORNITHINE; ISOLEUCINE; TYROSINE; THREONINE; TRYPTOPHAN; PHENYLALANINE; PROLINE; HISTIDINE

Drug Facts

ACTIVE INGREDIENT

witch hazel

INACTIVE INGREDIENT

water, cyclopentasiloxane, butylene glycol, betula alba juice, dimethicone, sodium chloride, peg/ppg-18/18 dimethicone, peg/ppg-19/18 dimethicone, olive fruit oil, magnolia kobus bark extract, torreya nucifera extract, cornus kousa extract, rosa multiflora fruit extract, chloranthus glaber extract, musa basjoo extract, acetyl hexapeptide 8, allantoin palmitoyl oligopeptide, palmitoyl tetrapeptide 7, human oligopeptide 1, willow bark extract, carmellia sinensis leaf extract, lavender oil, cymbopogon schoenanthus oil, abies sibirica oil, orange peel oil, amyris balsamifera bark oil, clary oil, grapefruit extract, tocopheryl acetate, propolis extract, thujopsis dolabrata branch extract, matricaria flower/leaf extract

PURPOSE

anti wrinkle care

keep out of reach of the children

INDICATIONS AND USAGE

Take out the proper amount with the built-in spatula and apply it to your face as massaging to be well absorbed.
Especially there would be better effect if you apply it frequently after laser treatment.

When using this product
- keep out of eyes, ears, and mouth. If contact occurs, rinse with plenty of cold water right away and contact a physician. If swallowing, drink plenty of water and contact a physician

DOSAGE AND ADMINISTRATION

for external use only